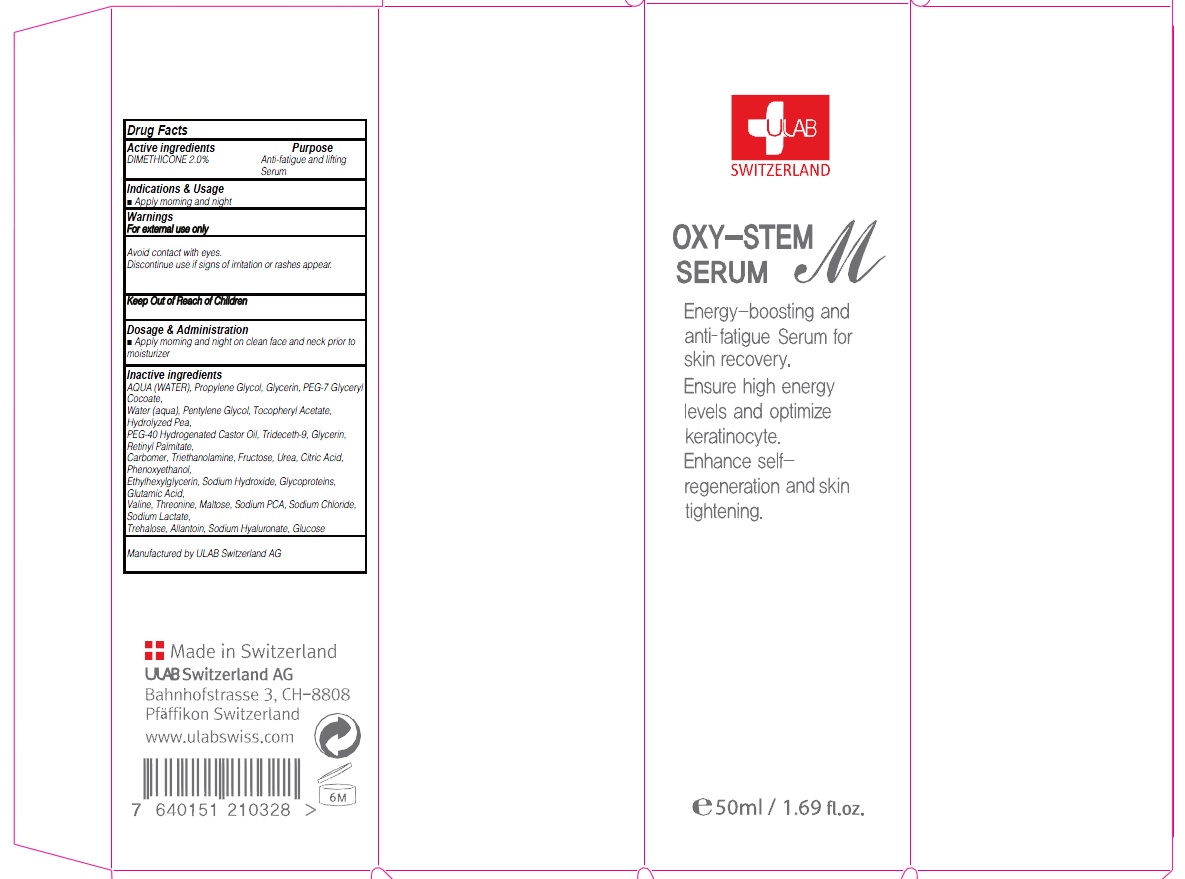 DRUG LABEL: OXY STEM M SERUM
NDC: 71276-070 | Form: CREAM
Manufacturer: ULAB
Category: otc | Type: HUMAN OTC DRUG LABEL
Date: 20170322

ACTIVE INGREDIENTS: DIMETHICONE 1.0 g/50 mL
INACTIVE INGREDIENTS: WATER; Propylene Glycol

ACTIVE INGREDIENT

Active ingredients: DIMETHICONE 2.0%

INACTIVE INGREDIENT

Inactive ingredients: AQUA (WATER), Propylene Glycol, Glycerin, PEG-7 Glyceryl Cocoate, Water (aqua), Pentylene Glycol, Tocopheryl Acetate, Hydrolyzed Pea, PEG-40 Hydrogenated Castor Oil, Trideceth-9, Glycerin, Retinyl Palmitate, Carbomer, Triethanolamine, Fructose, Urea, Citric Acid, Phenoxyethanol, Ethylhexylglycerin, Sodium Hydroxide, Glycoproteins, Glutamic Acid, Valine, Threonine, Maltose, Sodium PCA, Sodium Chloride, Sodium Lactate, Trehalose, Allantoin, Sodium Hyaluronate, Glucose

PURPOSE

Purpose: Anti-fatigue and lifting Serum

WARNINGS

Warnings: For external use only Avoid contact with eyes. Discontinue use if signs of irritation or rashes appear.

KEEP OUT OF REACH OF CHILDREN

INDICATIONS & USAGE

Indications & Usage: Apply morning and night

DOSAGE & ADMINISTRATION

Dosage & Administration: Apply morning and night on clean face and neck prior to moisturizer